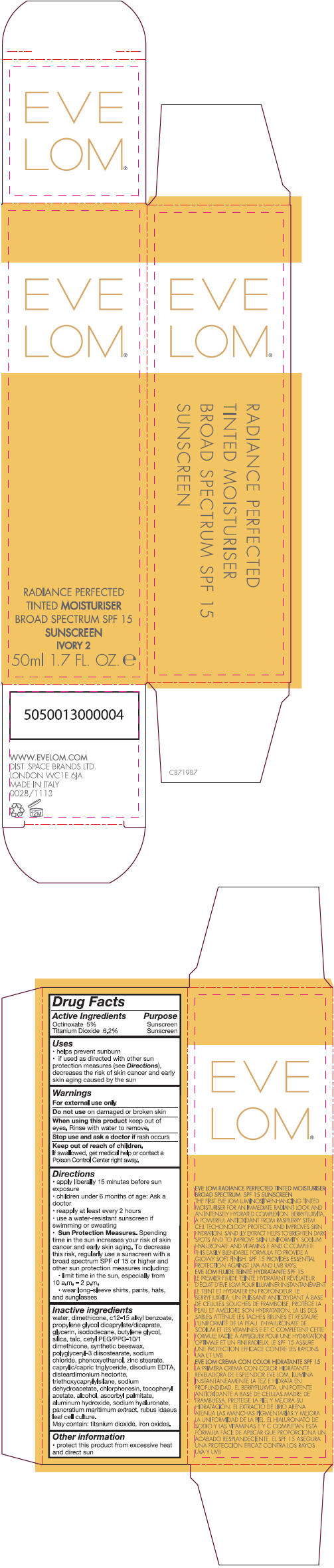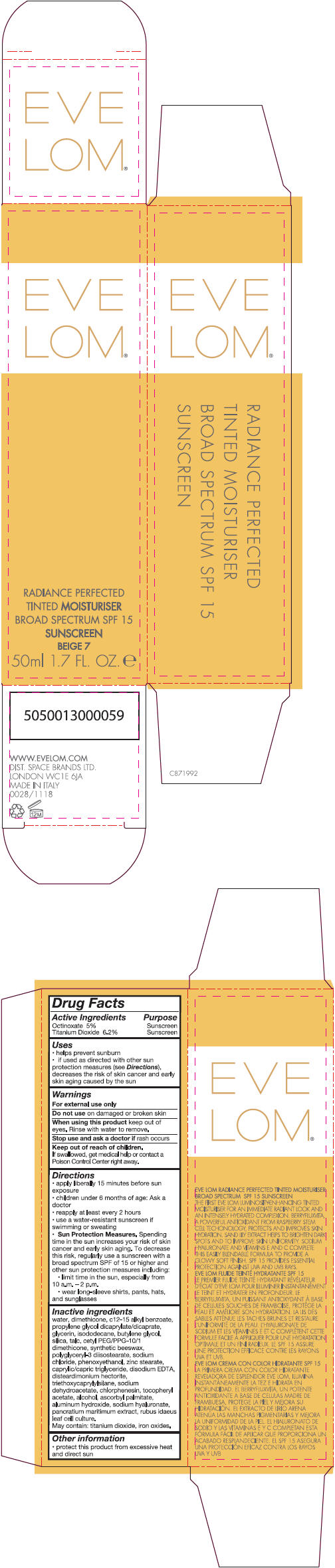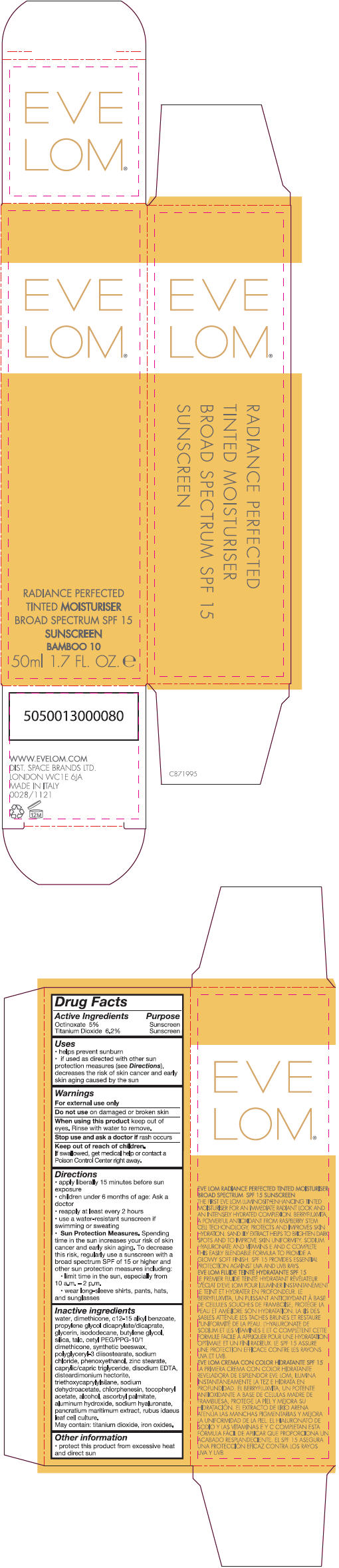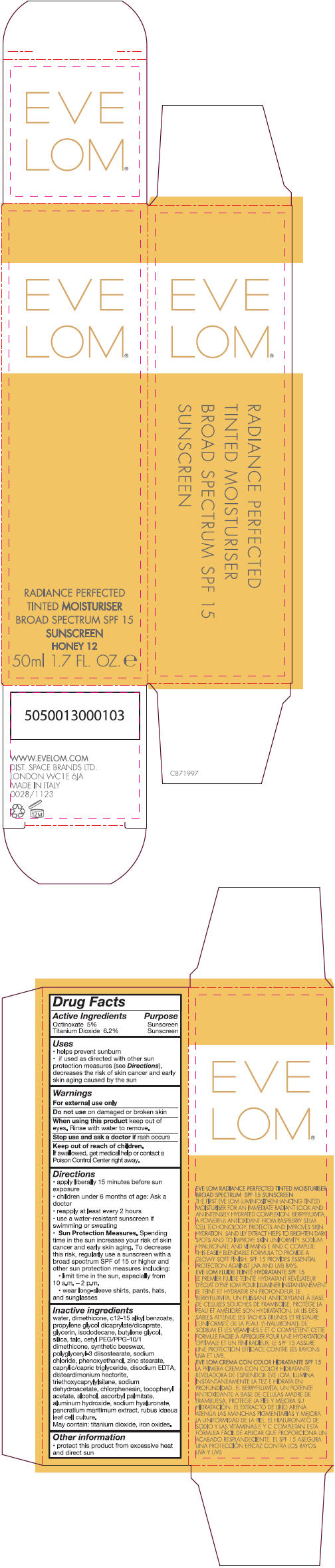 DRUG LABEL: Eve Lom Radiance Perfected Tinted Moisturiser SPF 15
NDC: 61601-1193 | Form: CREAM
Manufacturer: Space Brands Limited
Category: otc | Type: HUMAN OTC DRUG LABEL
Date: 20140228

ACTIVE INGREDIENTS: Titanium Dioxide 3.1 g/50 mL; Octinoxate 2.5 g/50 mL
INACTIVE INGREDIENTS: Water; Dimethicone; Alkyl (C12-15) Benzoate; Propylene Glycol Dicaprylate/Dicaprate; Glycerin; Isododecane; Butylene Glycol; Silicon Dioxide; Talc; Cetyl PEG/PPG-10/1 Dimethicone (HLB 2); Polyglyceryl-3 Diisostearate; Sodium Chloride; Ferric Oxide Yellow; Phenoxyethanol; Zinc Stearate; Medium-Chain Triglycerides; Edetate Sodium; Disteardimonium Hectorite; Triethoxycaprylylsilane; Sodium Dehydroacetate; Chlorphenesin; .Alpha.-Tocopherol Acetate; Alcohol; Aluminum Hydroxide; Ferric Oxide Red; Ascorbyl Palmitate; Ferrosoferric Oxide; Hyaluronate Sodium

Eve Lom® Radiance Perfected Tinted Moisturiser SPF 15

Drug Facts

ACTIVE INGREDIENT

Active Ingredients | Purpose
Octinoxate 5% | Sunscreen
Titanium Dioxide 6.2% | Sunscreen

Uses

- helps prevent sunburn
- if used as directed with other sun protection measure (see Directions), decreases the risk of skin cancer and early skin aging caused by the sun

Warnings

For external use only

Do not use on damaged or broken skin

When using this product keep out of eyes. Rinse with water to remove.

Stop use and ask a doctor if rash occurs.

Keep out of reach of children. If swallowed, get medical help or contact a Poison Control Center right away.

Directions

- apply liberally 15 minutes before sun exposure
- children under 6 months of age: Ask a doctor
- reapply at least every 2 hours
- use a water-resistant sunscreen if swimming or sweating
- Sun Protection Measures. Spending time in the sun increases your risk of skin cancer and early skin aging. To decrease this risk, regularly use a sunscreen with a broad spectrum SPF of 15 or higher and other sun protection measures including:
  - limit time in the sun, especially from 10 a.m. – 2 p.m.
  - wear long-sleeve shirts, pants, hats, and sunglasses

Inactive ingredients

water, dimethicone, c 12-15 alkly benzoate, propylene glycol dicaprylate/dicaprate, glycerin, isododecane, butylene glycol, silica, talc, cetyl PEG/PPG-10/1 dimethicone, synthetic beeswax, polyglyceryl-3 diisostearate, sodium chloride, phenoxyethanol, zinc stearate, caprylic/capric triglyceride, disodium EDTA, disteardimonium hectorite, triethoxycaprylylsilane, sodium dehydroacetate, chlorphenesin, tocopheryl acetate, alcohol, ascorbyl palmitate, aluminum hydroxide, sodium hyaluronate, pancratium maritimum extract, rubus idaeus leaf cell culture.

May contain: titanium dioxide, iron oxides.

Other information

- protect this product from excessive heat and direct sun

PRINCIPAL DISPLAY PANEL - 50 ml Tube Carton - Ivory 2

EVE
LOM®

RADIANCE PERFECTED
TINTED MOISTURISER
BROAD SPECTRUM SPF 15
SUNSCREEN
IVORY 2
50ml 1.7 FL. OZ. e

PRINCIPAL DISPLAY PANEL - 50 ml Tube Carton - Beige 7

EVE
LOM®

RADIANCE PERFECTED
TINTED MOISTURISER
BROAD SPECTRUM SPF 15
SUNSCREEN
BEIGE 7
50ml 1.7 FL. OZ. e

PRINCIPAL DISPLAY PANEL - 50 ml Tube Carton - Bamboo 10

EVE
LOM®

RADIANCE PERFECTED
TINTED MOISTURISER
BROAD SPECTRUM SPF 15
SUNSCREEN
BAMBOO 10
50ml 1.7 FL. OZ. e

PRINCIPAL DISPLAY PANEL - 50 ml Tube Carton - Honey 12

EVE
LOM®

RADIANCE PERFECTED
TINTED MOISTURISER
BROAD SPECTRUM SPF 15
SUNSCREEN
HONEY 12
50ml 1.7 FL. OZ. e